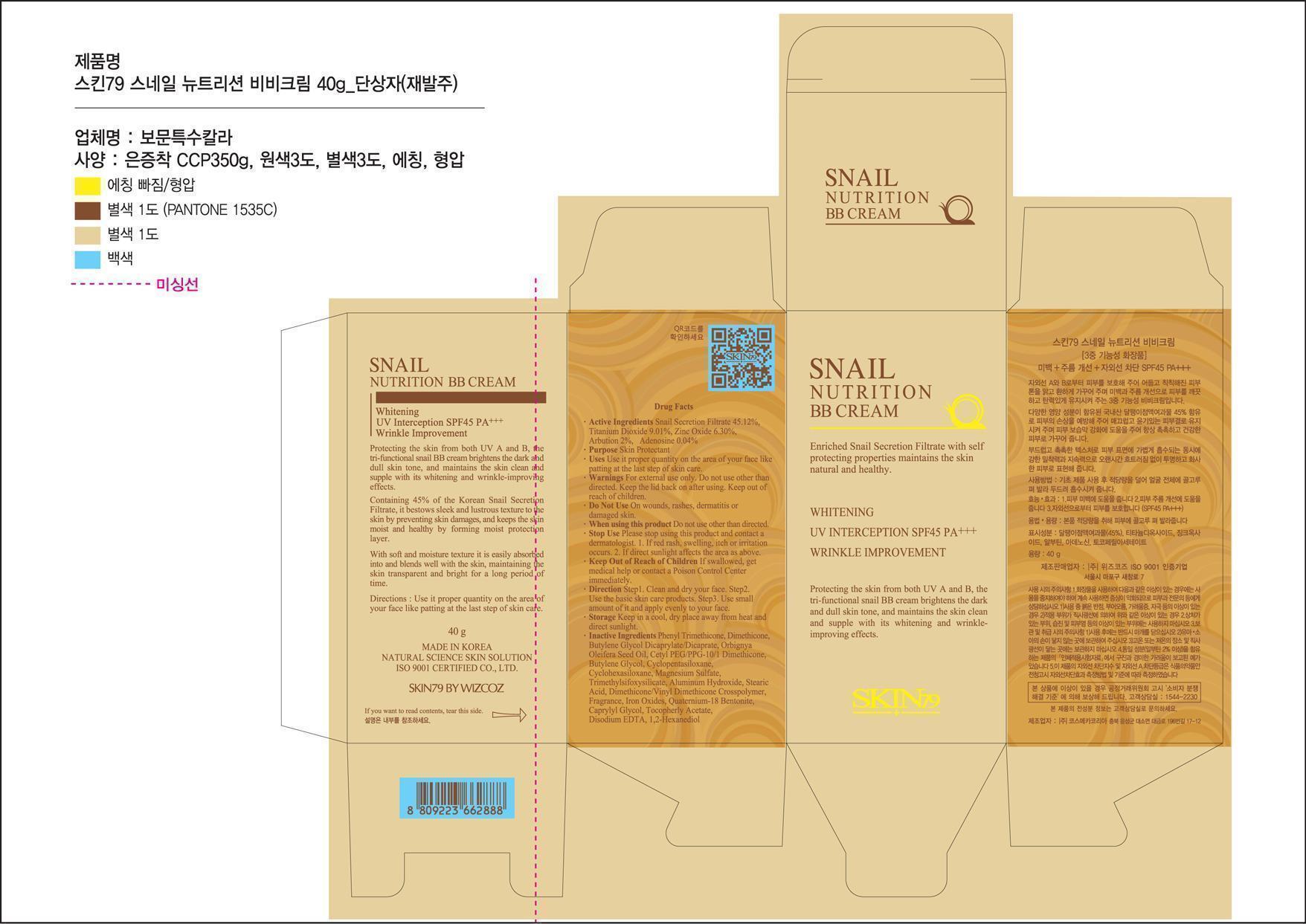 DRUG LABEL: SKIN79 SNAIL NUTRITION BBCREAM
NDC: 49715-019 | Form: CREAM
Manufacturer: WIZCOZ CORPORATION LTD
Category: otc | Type: HUMAN OTC DRUG LABEL
Date: 20130306

ACTIVE INGREDIENTS: SNAIL, UNSPECIFIED 18.05 g/40 g; TITANIUM DIOXIDE 3.6 g/40 g; ZINC OXIDE 2.52 g/40 g; ARBUTIN 0.8 g/40 g; ADENOSINE 0.016 g/40 g
INACTIVE INGREDIENTS: PHENYL TRIMETHICONE; DIMETHICONE; BUTYLENE GLYCOL DICAPRYLATE/DICAPRATE; CETYL PEG/PPG-10/1 DIMETHICONE (HLB 2); BUTYLENE GLYCOL; CYCLOMETHICONE 5; CYCLOMETHICONE 6; MAGNESIUM SULFATE; TRIMETHYLSILOXYSILICATE (M/Q 0.6-0.8); ALUMINUM HYDROXIDE; STEARIC ACID; DIMETHICONE/VINYL DIMETHICONE CROSSPOLYMER (SOFT PARTICLE); BROWN IRON OXIDE; QUATERNIUM-18; BENTONITE; CAPRYLYL GLYCOL; .ALPHA.-TOCOPHEROL ACETATE; EDETATE DISODIUM; 1,2-HEXANEDIOL

ACTIVE INGREDIENT

Active ingredients: Snail Secretion Filtrate 45.12%, Titanium Dioxide 9.01%, Zinc Oxide 6.30%, Arbutin 2%, Adenosine 0.04%

Purpose: Skin Protectant

INACTIVE INGREDIENT

Inactive Ingredients:Phenyl Trimethicone, Dimethicone, Butylene Glycol Dicaprylate/Dicaprate, Orbignya Oleifera Seed Oil, Cetyl PEG/PPG-10/1 Dimethicone, Butylene Glycol, Cyclopentasiloxane, Cyclohexasiloxane, Magnesium Sulfate, Trimethylsiloxysilicate, , Aluminum Hydroxide, Stearic Acid, Dimethicone/Vinyl Dimethicone Crosspolymer, Fragrance, Iron Oxide, Quaternium-18, Bentonite, Caprylyl Glycol, Tocopherol Acetate, Disodium EDTA